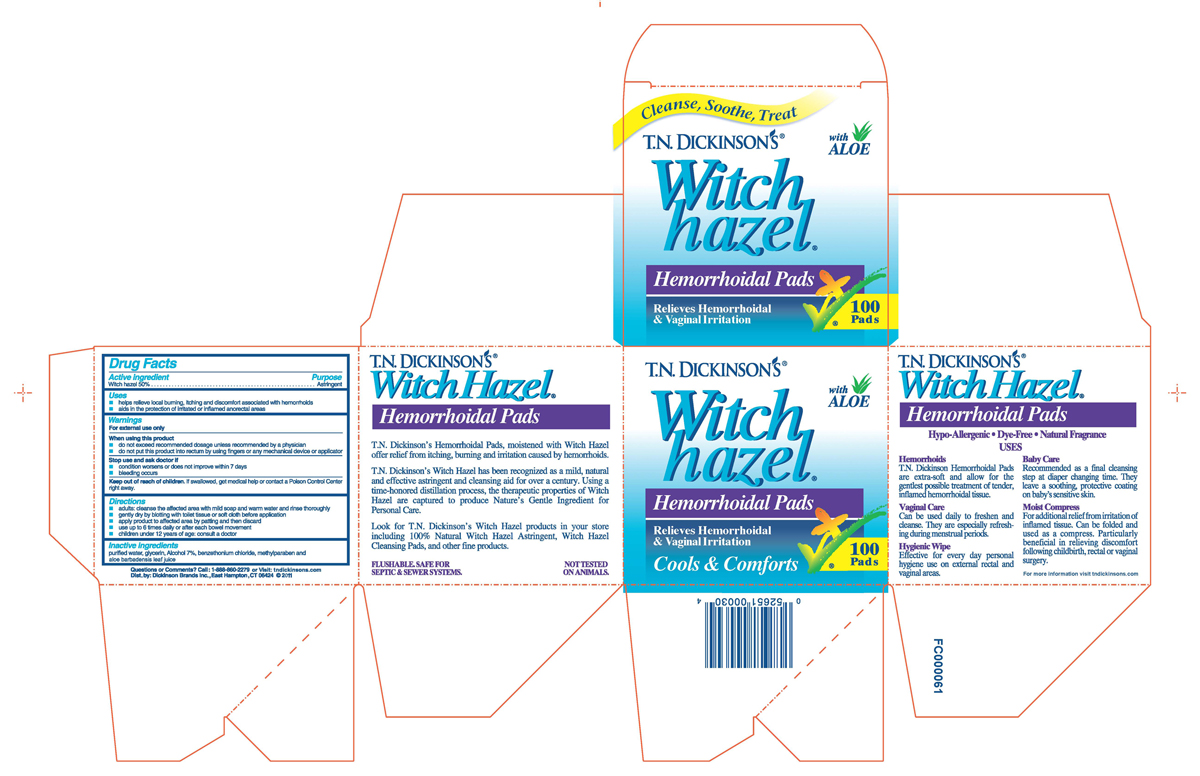 DRUG LABEL: TN Dickinsons Witch Hazel Hemorrhoidal Pads
NDC: 52651-003 | Form: CLOTH
Manufacturer: Dickinson Brands Inc.
Category: otc | Type: HUMAN OTC DRUG LABEL
Date: 20241218

ACTIVE INGREDIENTS: WITCH HAZEL 1.2 g/1 1
INACTIVE INGREDIENTS: WATER; GLYCERIN; ALCOHOL; BENZETHONIUM CHLORIDE; METHYLPARABEN; ALOE VERA LEAF

Drug Facts

Active ingredient
Witch hazel 50%

Purpose

Astringent

Uses

- helps relieve local burning, itching, and discomfort associated with hemorrhoids
- aids in the protection of irritated or inflamed anorectal areas

Warnings:

For external use only

When using this product

- do not exceed recommended dosage unless recommended by a physician
- do not put this product into rectum by using fingers or any mechanical device or applicator

Stop use and ask doctor if

- condition worsens or does not improve within 7 days
- bleeding occurs

Keep out of reach of children. If swallowed, get medical
help or contact Poison Control Center right away.

Directions

- adults: cleanse the affected area with mild soap and warm water and rinse thoroughly
- gently dry by blotting with toilet tissue or soft cloth before application
- apply product to affected area by patting and then discard
- use up to 6 times daily or after each bowel movement
- children under 12 years of age:consult a doctor

Inactive ingredients

purified water, glycerin, Alcohol 7%, benzethonium chloride, methylparaben, and aloe barbadensis leaf juice

Questions or Comments? Call toll free: 1-888-860-2279 or Visit tndickinsons.com
Dist. by: Dickinson Brands Inc, East Hampton, CT 06424

Product Packaging

Cleanse, Soothe Treat

T.N. DICKINSON'S Witch hazel

Hemorrhoidal Pads with Aloe

Relieves Hemorrhoidal
and Vaginal Irritation

Cools and Comforts